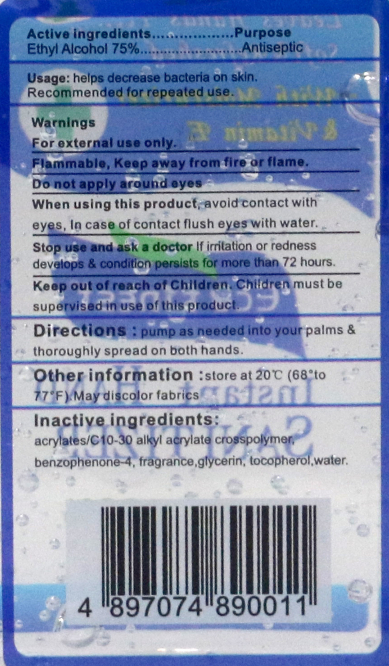 DRUG LABEL: Instant Hand Sanitizer
NDC: 54237-001 | Form: LIQUID
Manufacturer: Guangzhou Daieme Cosmetic Co,.Ltd
Category: otc | Type: HUMAN OTC DRUG LABEL
Date: 20230309

ACTIVE INGREDIENTS: ALCOHOL 42 mL/60 mL
INACTIVE INGREDIENTS: ALOE; TOCOPHEROL; GLYCERIN; SULISOBENZONE; CARBOMER COPOLYMER TYPE A (ALLYL PENTAERYTHRITOL CROSSLINKED); WATER

DOSAGE AND ADMINISTRATION

store at 20C (68° to 77°F). May discolor fabrics

ACTIVE INGREDIENT

Ethyl Alcohol

keep out of reach of children section

WARNINGS

For external use only.
Flammable, Keep away fromfireor flame.
DO not apply around eyes.

INACTIVE INGREDIENT

acrylates/C10-30 alkyl acrylate crosspolymer,benzophenone 4, fragrance,glycerin, tocopherol,water.

PURPOSE

Disinfection
Sterilization
No Rinseing

When using this product, avoid contact with eyes, In case of contact flush eyes with water.

Stop use and ask a doctor If iiation or redness develops & condition persists for more than72 hours.